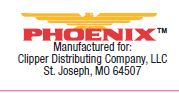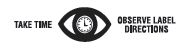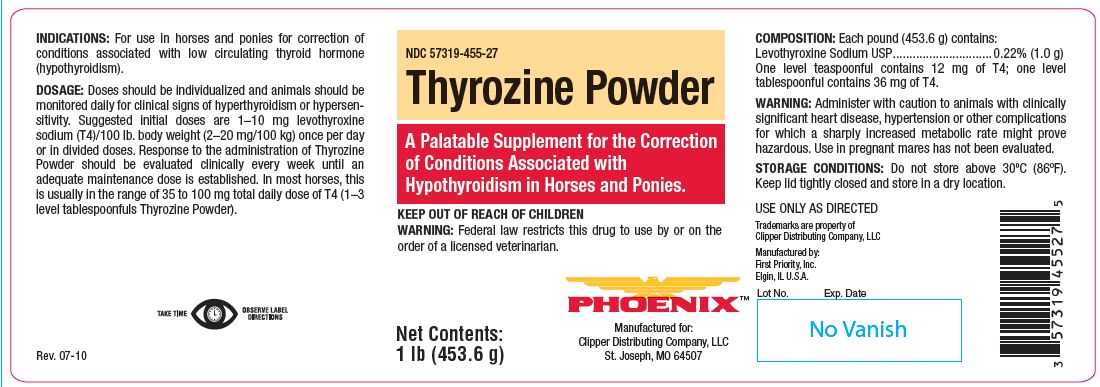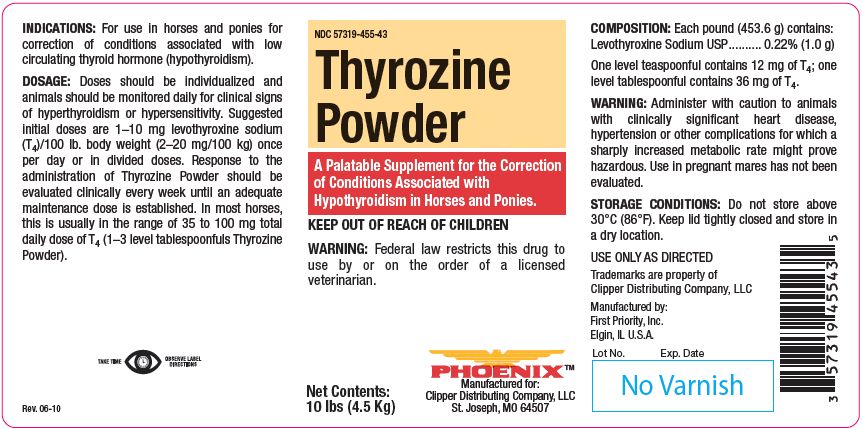 DRUG LABEL: Thyrozine
NDC: 57319-455 | Form: POWDER
Manufacturer: PHOENIX PHARMACEUTICAL INC./ CLIPPER DISTRIBUTING, INC.
Category: animal | Type: OTC ANIMAL DRUG LABEL
Date: 20180119

ACTIVE INGREDIENTS: LEVOTHYROXINE SODIUM ANHYDROUS 1 g/453.6 g

Thyrozine Powder

PURPOSE

A Palatable Supplement for the Correction of Conditions Associated with Hypothyroidism in Horses and Ponies.

KEEP OUT OF REACH OF CHILDREN
WARNING: Federal law restricts this drug to use by or on the order of a licensed veterinarian.

INDICATIONS:

For use in horses and ponies for correction of conditions associated with low circulating thyroid hormone (hypothyroidism).

DOSAGE:

Doses should be individualized and animals should be monitored daily for clinical signs of hyperthyroidism or hypersensitivity. Suggested
initial doses are 1–10 mg levothyroxine sodium (T4)/100 lb. body weight (2–20 mg/100 kg) once per day or in divided doses. Response to the administration of Thyrozine Powder should be evaluated clinically every week until an adequate maintenance dose is established. In most horses, this is usually in the range of 35 to 100 mg total daily dose of T4 (1–3 level tablespoonfuls Thyrozine Powder).

COMPOSITION:

Each pound (453.6 g) contains:
Levothyroxine Sodium USP.......... 0.22% (1.0 g)
One level teaspoonful contains 12 mg of T4; one level tablespoonful contains 36 mg of T4.

WARNING:

Administer with caution to animals with clinically significant heart disease, hypertension or other complications for which a sharply increased metabolic rate might prove hazardous. Use in pregnant mares has not been evaluated.

STORAGE CONDITIONS:

Do not store above 30°C (86°F). Keep lid tightly closed and store in a dry location.
USE ONLY AS DIRECTED

Net Contents:

1 lb (453.6 g)

10 lbs (4.5 Kg)

INFORMATION FOR OWNERS/CAREGIVERS

Trademarks are property of Clipper Distributing Company, LLC
Manufactured by:
First Priority, Inc.
Elgin, IL U.S.A.